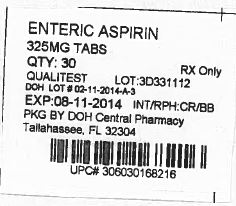 DRUG LABEL: Aspirin
NDC: 53808-1028 | Form: TABLET
Manufacturer: State of Florida DOH Central Pharmacy
Category: otc | Type: HUMAN OTC DRUG LABEL
Date: 20150103

ACTIVE INGREDIENTS: ASPIRIN 325 mg/1 1
INACTIVE INGREDIENTS: CROSCARMELLOSE SODIUM; HYDROXYPROPYL CELLULOSE (TYPE H); STARCH, CORN; D&C YELLOW NO. 10; HYPROMELLOSE PHTHALATE (31% PHTHALATE, 40 CST); CELLULOSE, MICROCRYSTALLINE; POLYSORBATE 80; MINERAL OIL; POLYETHYLENE GLYCOL 400; TITANIUM DIOXIDE; FD&C YELLOW NO. 6

Regular Strength Enteric Anti-inflammatory/Analgesic Aspirin

ACTIVE INGREDIENT (IN EACH TABLET)

Aspirin 325 mg (NSAID*)

*nonsteroidal anti-inflammatory drug

PURPOSE

Pain reliever

USES

for the temporary relief of minor aches and pains or as recommended by your doctor. Because of its delayed action, this product will not provide fast relief of headaches or other symptoms needing immediate relief.

WARNINGS

Reye’s syndrome: Children and teenagers who have or are recovering from chicken pox or flu-like symptoms should not use this product. When using this product, if changes in behavior with nausea and vomiting occur, consult a doctor because these symptoms could be an early sign of Reye’s syndrome, a rare but serious illness.

Allergy alert: Aspirin may cause a severe allergic reaction which may include: ■ hives ■facial swelling ■ asthma (wheezing) ■ shock

Stomach bleeding warning: This product contains an NSAID, which may cause severe stomach bleeding. The chance is higher if you ■ are age 60 or older ■ have had stomach ulcers or bleeding problems ■ take a blood thinning (anticoagulant) or steroid drug ■ take other drugs containing prescription or nonprescription NSAIDS (aspirin, ibuprofen, naproxen or others) ■ have 3 or more alcoholic drinks every day while using this product ■ take more or for a longer time than directed

Do not use

if you are allergic to aspirin or other pain relievers/fever reducers

Ask a doctor before use if

■ stomach bleeding warning applies to you ■ you have a history of stomach problems, such as heartburn ■ you have high blood pressure, heart disease, liver cirrhosis, or kidney disease ■ you have asthma ■ you are taking a diuretic

Ask a doctor or pharmacist before use if you are

taking a prescription drug for ■ anticoagulation (thinning the blood) ■ diabetes ■ gout ■ arthritis

Stop use and ask a doctor if

■ an allergic reaction occurs. Seek medical help right away ■ you experience any of the following signs of stomach bleeding: feel faint, vomit blood, have bloody or black stools, have stomach pain that does not get better ■ new symptoms occur ■ redness or swelling is present ■ ringing in the ears or loss of hearing occurs ■ pain gets worse or lasts for more than 10 days

If pregnant or breast-feeding,

ask a health professional before use. It is especially important not to use aspirin during the last 3 months of pregnancy unless specifically directed to do so by a doctor because it may cause problems in the unborn child or complications during delivery.

Keep out of reach of children.

In case of overdose, get medical help or contact a Poison Control Center right away.

Directions

■ drink a full glass of water with each does ■ adults and children 12 years and over: take 1 to 2 tablets every 4 hours not to exceed 12 tablets in 24 hours unless directed by a doctor ■ children under 12 years: consult a doctor

Other information

■ store at room temperature ■ do not use if imprinted safety seal under cap is broken or missing

You may report serious side effects to 1-888-952-0050

Inactive ingredients

Acetylated monoglycerides, corn starch, croscarmellose sodium, D&C Yellow 10, FD&C Yellow #6, hypromellose, hypromellose phthalate, microcrystalline cellulose, mineral oil, polyethylene glycol 400, polysorbate 80, titanium doxide

How Supplied

Aspirin is supplied by State of Florida DOH Central Pharmacy as follows:

NDC | Strength | Quantity/Form | Color | Source Prod. Code
53808-1028-1 | 325 MG | 30 Tablets in a Blister Pack | ORANGE | 0603-0168

This Product was Repackaged By:

State of Florida DOH Central Pharmacy
104-2 Hamilton Park Drive
Tallahassee, FL 32304
USA

PACKAGE LABEL

Label Image for 53808-1028
325mg